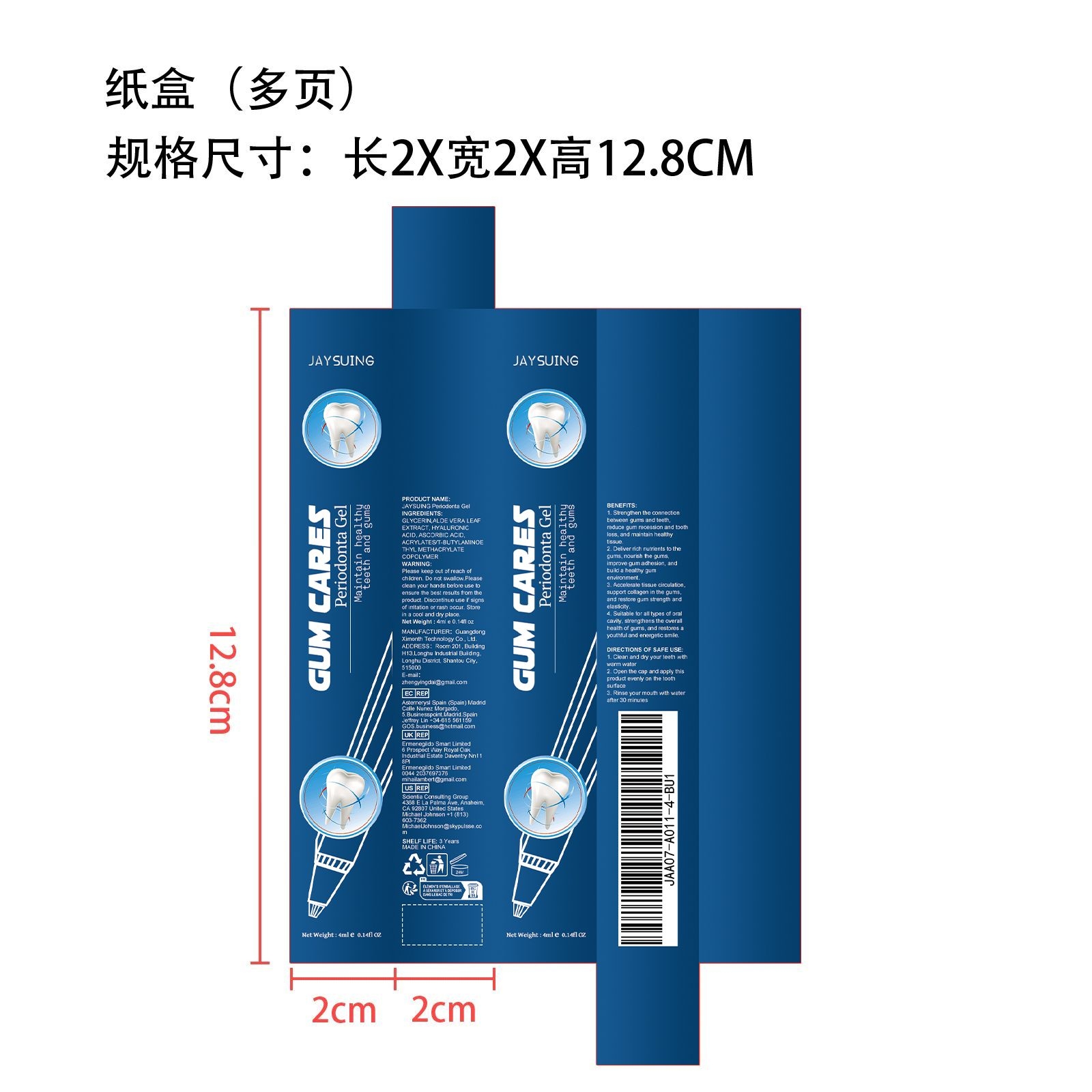 DRUG LABEL: Periodonta Gel
NDC: 84660-015 | Form: GEL
Manufacturer: Guangdong Ximonth Technology Co., Ltd.
Category: otc | Type: HUMAN OTC DRUG LABEL
Date: 20240909

ACTIVE INGREDIENTS: ALOE VERA LEAF 1 mg/4 mg; ASCORBIC ACID 0.6 mg/4 mg; ACRYLIC ACID 0.4 mg/4 mg
INACTIVE INGREDIENTS: GLYCERIN 1.2 mg/4 mg; HYALURONIC ACID 0.8 mg/4 mg

Active Ingredient(s)

ALOE VERA LEAF EXTRACT、HYALURONIC ACID、ASCORBIC ACID、ACRYLATES/T-BUTYLAMIN OETHYL METHACRYLATE COPOLYMER

Purpose

Reduce gum recession and tooth loss, ard maintan healthy tissue.

Use

1. Clean and dry your teeth withwarm water. 2. Open the cap and apply this product evenly on the tooth surface. 3. Rinse your mouth with water after 30 minutes.

Do not use

Discontinue use if signs of irritation or rash occur.

STOP USE

Discontinue use if signs of irritation or rash occur.

Warnings

Please keep out of reach of children.Do not swallow.Please clean your hands before use to ensure the best results from the product.Discontinue use if signs of irritation or rash occur.Store in a cool and dry place.

KEEP OUT OF REACH OF CHILDREN

Please keep out of reach of children. Do not swallow.

STORAGE AND HANDLING

Avoid freezing and excessive heat above 40C (104F) ）

Store in a cool and dry place.

INACTIVE INGREDIENT

GLYCERIN